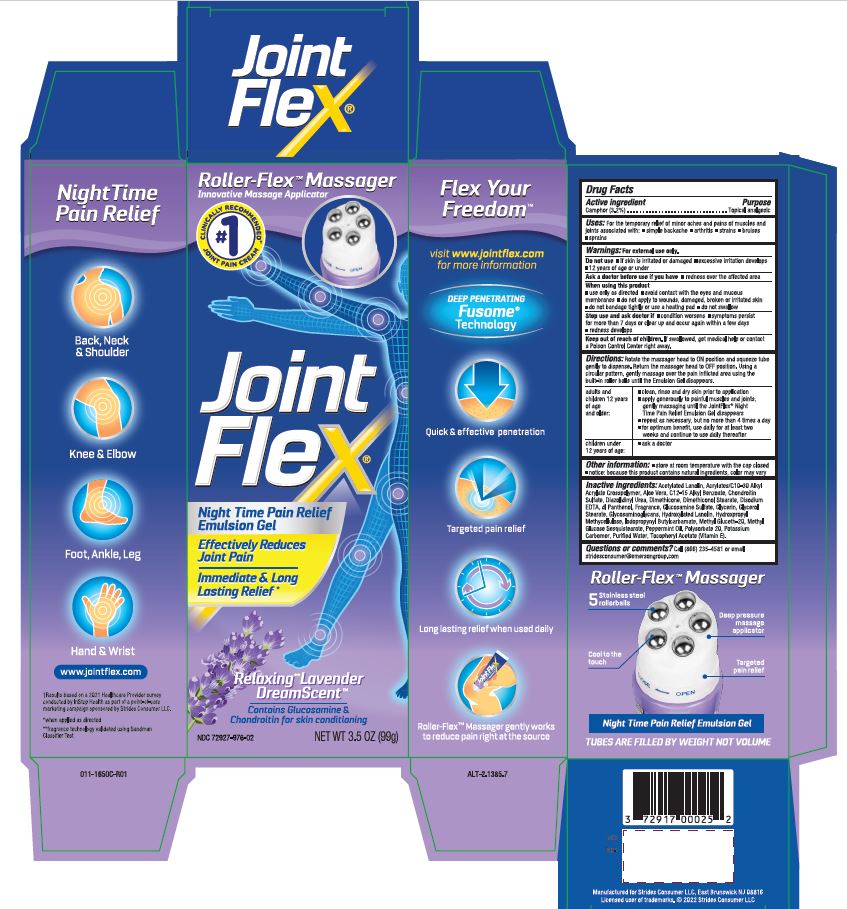 DRUG LABEL: Jointflex
NDC: 72927-976 | Form: CREAM
Manufacturer: Strides Consumer LLC
Category: otc | Type: HUMAN OTC DRUG LABEL
Date: 20250409

ACTIVE INGREDIENTS: CAMPHOR (SYNTHETIC) 3.2 g/100 g
INACTIVE INGREDIENTS: ACETYLATED LANOLIN; ALKYL (C12-15) BENZOATE; ALOE VERA LEAF; ALPHA-TOCOPHEROL ACETATE; CARBOMER 1342; CARBOMER INTERPOLYMER TYPE A (55000 CPS); CHONDROITIN SULFATE (SHARK); DIAZOLIDINYL UREA; DIMETHICONE; EDETATE DISODIUM; GLUCOSAMINE SULFATE POTASSIUM CHLORIDE; GLYCERIN; GLYCERYL MONOSTEARATE; HYDROXYLATED LANOLIN; HYPROMELLOSES; IODOPROPYNYL BUTYLCARBAMATE; METHYL GLUCETH-20; METHYL GLUCOSE SESQUISTEARATE; PANTHENOL; PEPPERMINT OIL; POLYOXYL 40 STEARATE; POLYSORBATE 20; POTASSIUM HYDROXIDE; SHARK CARTILAGE; WATER

JOINTFLEX NightTime Pain Relief
Drug Facts

Active ingredient

Camphor (3.2%)

Purpose

Topical analgesic

Uses:

For the temporary relief of minor aches and pains of muscles and joints associated with:

- simple backache
- arthritis
- strains
- bruises
- sprains

Warnings:

For external use only.

Do not use

- if skin is irritated or damaged
- excessive irritation develops
- 12 years of age or under

Ask a doctor befor use if you have

- redness over the affected area

When using this product

- use only as directed
- avoid contact with the eyes and mucous membranes
- do not apply to wounds, damaged, broken or irritated skin
- do not bandage tightly or use a heating pad
- do not swallow

Stop use and ask doctor if

- condition worsens
- symptoms persist for more than 7 days or clear up and occur again within a few days
- redness develops

Keep out of reach of children.

If swallowed, get medical help or contact a Poison Control Center right away.

Directions:

Rotate the massager head to ON position and squeeze tube gently to dispense. Return the massager head to OFF position. Using a circular pattern, gently massage over the pain inflicted area using the built-in roller balls until the Emulsion Gel disappears.

adults and children 12 years of age and older: | - clean, rinse and dry skin prior to application - apply generously to painful muscles and joints, gently massaging until the JointFlex® Night Time Pain Relief Emulsion Gel disappears - repeat as necessary, but no more than 4 times a day - for optimum benefit, use daily for at least two weeks and continue to use daily thereafter
children under 12 years of age: | - ask a doctor

Other information:

- store at room temperature with the cap closed
- notice: because this product contains natural ingredients, color may vary

Inactive ingredients:

Acetylated Lanolin, Acrylates/C10-30 Alkyl Acrylate Crosspolymer, Aloe Vera, C12-15 Alkyl Benzoate, Chondroitin Sulfate, Diazolidinyl Urea, Dimethicone, Dimethiconol Stearate, Disodium EDTA, dl Panthenol, Fragrance, Glucosamine Sulfate, Glycerin, Glycerol Stearate, Glycosaminoglycans, Hydroxylated Lanolin, Hydroxpropyl Methycellulose, Iodopropynyl Butylcarbamate, Methyl Gluceth-20, Methyl Glucose Sesquistearate, Peppermint Oil, Polysorbate 20, Potassium Carbomer, Purified Water, Tocopheryl Acetate (Vitamin E).

Questions or comments?

Call (866) 235-4581 or email stridesconsumer@emersongroup.com

Manufactured for

Strides Consumer LLC,

East Brunswick, NJ 08816

Licensed user of trademarks. ©2022 Strides Consumer LLC

†Results based on a 2021 Healthcare Provider survey conducted by InStep Health as part of a point-of-care marketing campaign sponsored by Strides Consumer LLC.

www.jointflex.com

PACKAGE LABEL.PRINCIPAL DISPLAY PANEL

Flex Your FreedomTM

Visit www.jointflex.com for more information

DEEP PENETRATING Fusome® Technology

Quick & effective penetration

Targeted pain relief

Long lasting relief when used daily

Roller-FlexTM Massager gently works to reduce pain right at the source

Roller-FlexTMMassager

Innovative Massage Applicator

#1 CLINICALLY RECOMMENDED† JOINT PAIN CREAM

Effectively Reduces Joint Pain

Immediate & Long Lasting Relief*

Relaxing** Lavender DreamScentTM

Contains Glucosamine & Chondroitin for skin conditioning

NDC 72927-976-02

NET WT 3.5 OZ (99g)

Night Time Pain Relief

Back, Neck & Shoulde

Knee & Elbow

Foot, Ankle, Leg

Hand & Wrist

*When applied as directed

**fragrance technology validated using Sandman Classifier Test

Roller-FlexTMMassager

5 Stainless steel rollerballs

Deep pressure massage applicator

Cool to the touch

Targeted pain relief

Night Time Pain Relief Emulsion Gel

TUBES ARE FILLED BY WEIGHT NOT VOLUME

011-1650C-R01